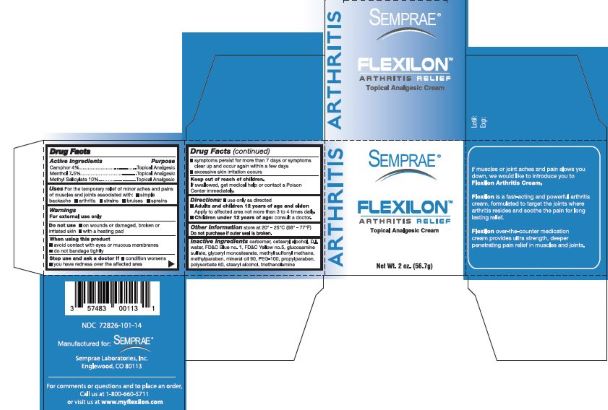 DRUG LABEL: Flexilon
NDC: 72826-101 | Form: CREAM
Manufacturer: Semprae Laboratories Inc
Category: otc | Type: HUMAN OTC DRUG LABEL
Date: 20221231

ACTIVE INGREDIENTS: MENTHOL 7.5 g/100 g; CAMPHOR (SYNTHETIC) 4 g/100 g; METHYL SALICYLATE 10 g/100 g
INACTIVE INGREDIENTS: WATER; CETOSTEARYL ALCOHOL; POLYSORBATE 60; GLYCERYL MONOSTEARATE; PEG-100 STEARATE; MINERAL OIL; METHYLPARABEN; PROPYLPARABEN; DIMETHYL SULFONE; TROLAMINE; CARBOMER 940; FD&C BLUE NO. 1; FD&C YELLOW NO. 5; GLUCOSAMINE SULFATE; STEARYL ALCOHOL

ACTIVE INGREDIENT

Camphor 4%

Menthol 7.5%

Methyl Salicylate 10%

PURPOSE

Topical analgesic

USES

For the temporary relief of minor aches and pains of muscles and joints associated with:

- simple backache
- arthritis
- strains
- bruises
- sprains

WARNINGS

For external use only

Do not use

- on wounds or damaged , broken or irritated skin
- with a heating pad

When using this product

- avoid contact with eyes or mucous membranes
- do not bandage tightly

Stop use and ask a doctor if

- condition worsens
- you have redness over the affected area
- symptoms persist for more than 7 days or symptoms clear up and occur within a few days
- excessive skin irritation occurs

Keep out of reach of children

If swallowed, get medical help or contact a Poison Center immediately

DIRECTIONS

- use only as directed
- Adults and children 12 years of age and older: Apply to affected area not more than 3 to 4 times daily.
- Children under 12 years of age: consult a doctor.

OTHER INFORMATION

store at 20-25C (68-77F)

Do not purchase if outer seal is broken

INACTIVE INGREDIENTS

carbomer, cetearyl alcohol, D.I. water, FD&C Blue no. 1, FD&C Yellow no.5, glucosamine sulfate, glyceryl monostearate, methyl sulfonyl methane,
methylparaben, mineral oil 90, PEG-100, propylparaben, polysorbate 60, stearyl alcohol, triethanolamine